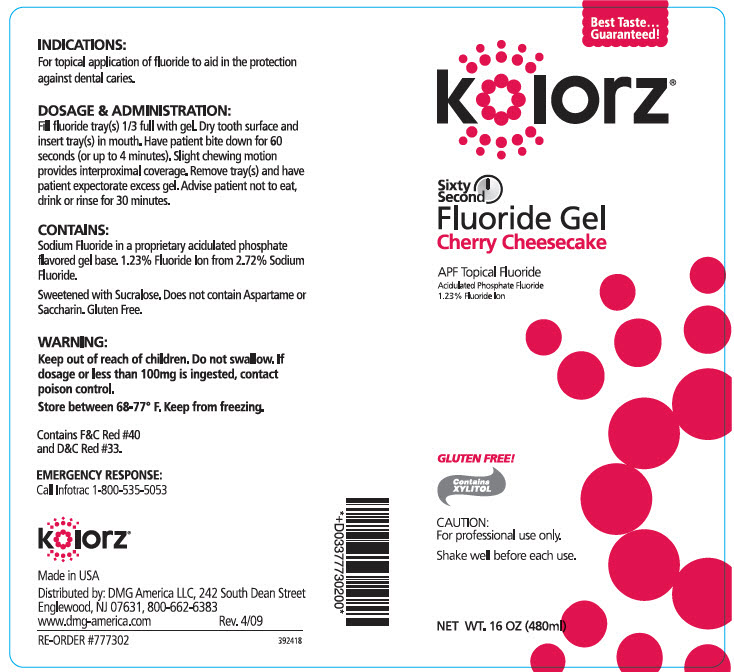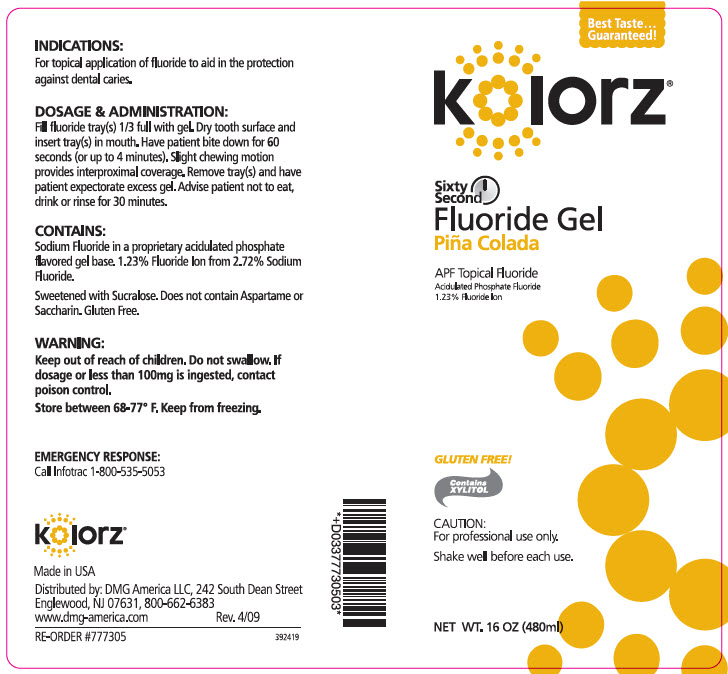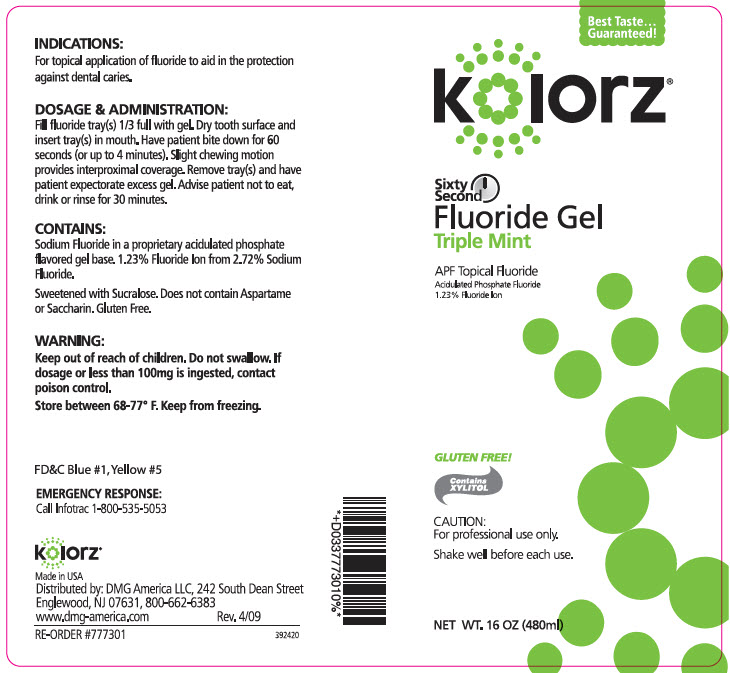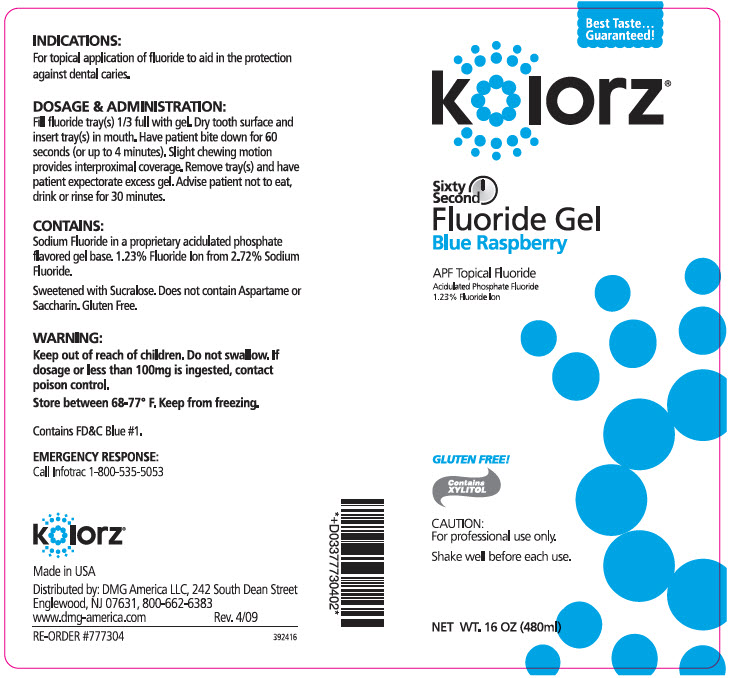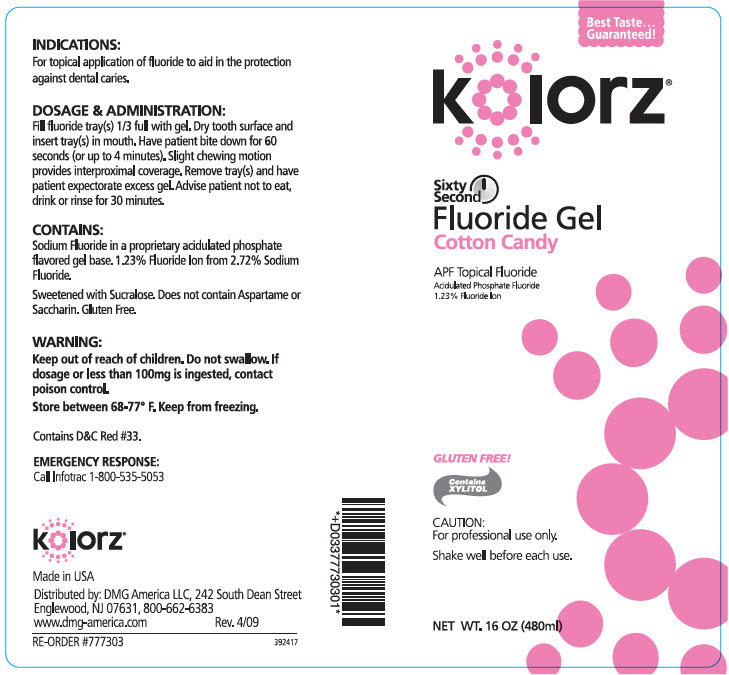 DRUG LABEL: KOLORZ SIXTY SECOND FLUORIDE
NDC: 25047-772 | Form: GEL
Manufacturer: DMG AMERICA, LLC
Category: prescription | Type: HUMAN PRESCRIPTION DRUG LABEL
Date: 20190328

ACTIVE INGREDIENTS: SODIUM FLUORIDE 12.3 mg/1 mL
INACTIVE INGREDIENTS: WATER; SUCRALOSE; XYLITOL; COCAMIDOPROPYL BETAINE

kolorz® Sixty Second Fluoride Gel

INDICATIONS

For topical application of fluoride to aid in the protection against dental caries.

DOSAGE & ADMINISTRATION

Fill fluoride tray(s) 1/3 full with gel. Dry tooth surface and insert tray(s) in mouth. Have patient bite down for 60 seconds (or up to 4 minutes). Slight chewing motion provides interproximal coverage. Remove tray(s) and have patient expectorate excess gel. Advise patient not to eat, drink or rinse for 30 minutes.

CONTAINS

Sodium Fluoride in a proprietary acidulated phosphate flavored gel base. 1.23% Fluoride Ion from 2.72% Sodium Fluoride.

Sweetened with Sucralose. Does not contain Aspartame or Saccharin. Gluten Free.

WARNING

Keep out of reach of children. Do not swallow. If dosage or less than 100mg is ingested, contact poison control.

STORAGE AND HANDLING

Store between 68-77° F. Keep from freezing.

Contains FD&C Blue #1.

EMERGENCY RESPONSE

Call Infotrac 1-800-535-5053

Made in USA

Distributed by :DMG America LLC, 242 South Dean Street
Englewood, NJ 07631, 800-662-6383
www.dmg-america.com
Rev. 4/09

RE-ORDER #777304
392415

PRINCIPAL DISPLAY PANEL - 480 ml Bottle Label - Cherry Cheesecake

Best Taste...
Guaranteed!

kolorz®

Sixty
Second
Fluoride Gel
Cherry Cheesecake

APF Topical Fluoride
Acidulated Phosphate Fluoride
1.23% Fluoride Ion

GLUTEN FREE!

Contains
XYLITOL

CAUTION:
For professional use only.

Shake well before each use.

NET WT. 16 OZ (480ml)

PRINCIPAL DISPLAY PANEL - 480 ml Bottle Label - Piña Colada

Best Taste...
Guaranteed!

kolorz®

Sixty
Second
Fluoride Gel
Piña Colada

APF Topical Fluoride
Acidulated Phosphate Fluoride
1.23% Fluoride Ion

GLUTEN FREE!

Contains
XYLITOL

CAUTION:
For professional use only.

Shake well before each use.

NET WT. 16 OZ (480ml)

PRINCIPAL DISPLAY PANEL - 480 ml Bottle Label - Triple Mint

Best Taste...
Guaranteed!

kolorz®

Sixty
Second
Fluoride Gel
Triple Mint

APF Topical Fluoride
Acidulated Phosphate Fluoride
1.23% Fluoride Ion

GLUTEN FREE!

Contains
XYLITOL

CAUTION:
For professional use only.

Shake well before each use.

NET WT. 16 OZ (480ml)

PRINCIPAL DISPLAY PANEL - 480 ml Bottle Label - Blue Raspberry

Best Taste...
Guaranteed!

kolorz®

Sixty
Second
Fluoride Gel
Blue Raspberry

APF Topical Fluoride
Acidulated Phosphate Fluoride
1.23% Fluoride Ion

GLUTEN FREE!

Contains
XYLITOL

CAUTION:
For professional use only.

Shake well before each use.

NET WT. 16 OZ (480ml)

PRINCIPAL DISPLAY PANEL - 480 ml Bottle Label - Cotton Candy

Best Taste...
Guaranteed!

kolorz®

Sixty
Second
Fluoride Gel
Cotton Candy

APF Topical Fluoride
Acidulated Phosphate Fluoride
1.23% Fluoride Ion

GLUTEN FREE!

Contains
XYLITOL

CAUTION:
For professional use only.

Shake well before each use.

NET WT. 16 OZ (480ml)